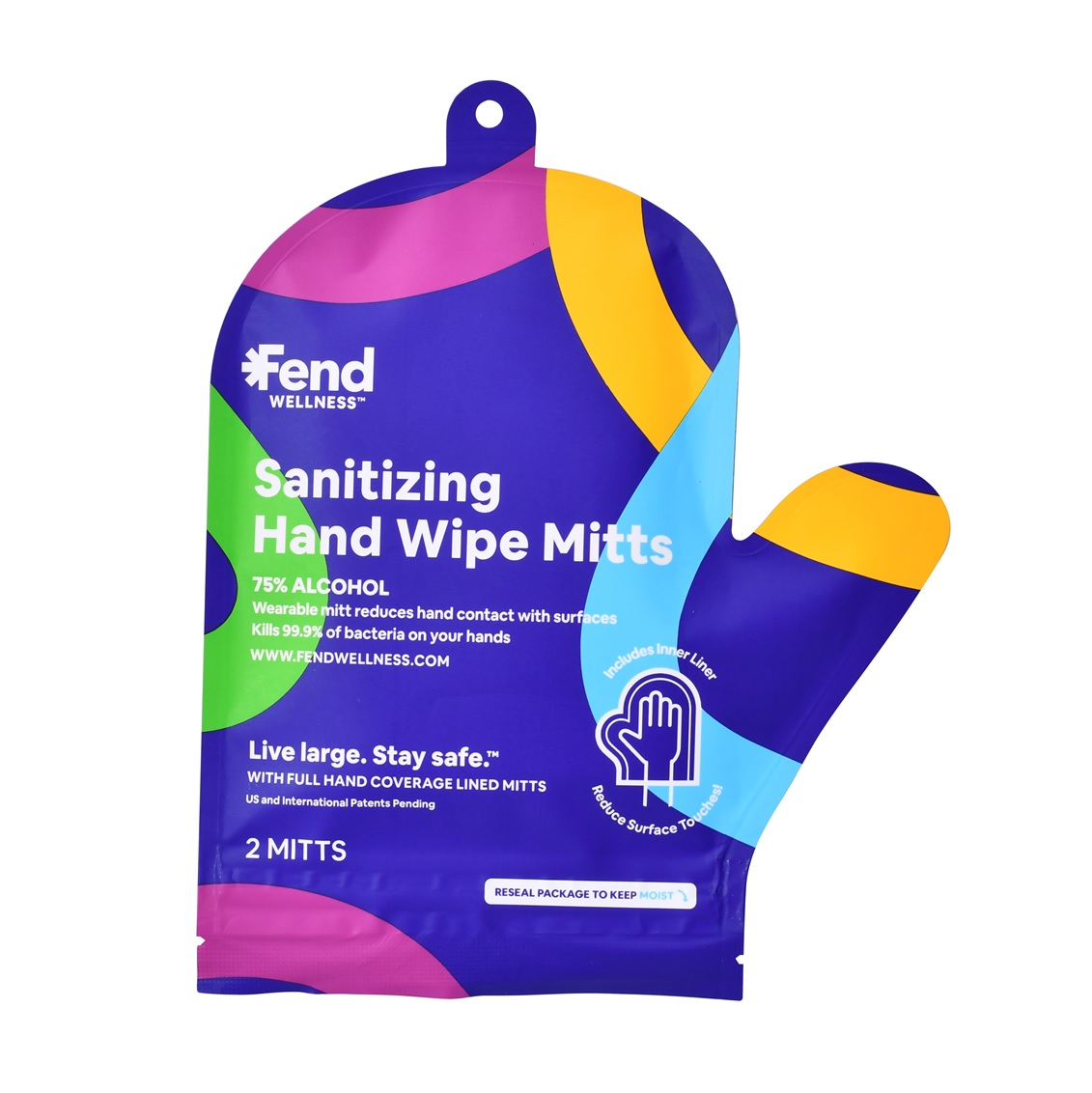 DRUG LABEL: Sanitizing Hand Wipe Mitts		
NDC: 77980-112 | Form: CLOTH
Manufacturer: Foshan Clean & Simple Cleaning Products Co., Ltd.
Category: otc | Type: HUMAN OTC DRUG LABEL
Date: 20210630

ACTIVE INGREDIENTS: ALCOHOL 24 mL/1 1
INACTIVE INGREDIENTS: WATER

Sanitizing Hand Wipe Mitts

Sanitizing Hand Wipe Mitts

Active Ingredient(s)

Alcohol 12ml/pcs. Purpose: Antiseptic

Purpose

Antiseptic, Sanitizing Hand Wipe Mitts

Use

Sanitizing Hand Wipe Mitts to help reduce bacteria that potentially can cause disease. For use when soap and water are not available.

Warnings

For external use only. Flammable. Keep away from heat or flame

Do not use

- in children less than 2 months of age
- on open skin wounds

When using this product keep out of eyes, ears, and mouth. In case of contact with eyes, rinse eyes thoroughly with water.
Stop use and ask a doctor if irritation or rash occurs. These may be signs of a serious condition.
Keep out of reach of children. If swallowed, get medical help or contact a Poison Control Center right away.

Stop use and ask a doctor if irritation or rash occurs. These may be signs of a serious condition.

Keep out of reach of children. If swallowed, get medical help or contact a Poison Control Center right away.

Directions

- Wipe the surface of the skin and let it dry naturally

Other information

- Store between 15-30C (59-86F)
- Avoid freezing and excessive heat above 40C (104F)

Inactive ingredients

purified water USP